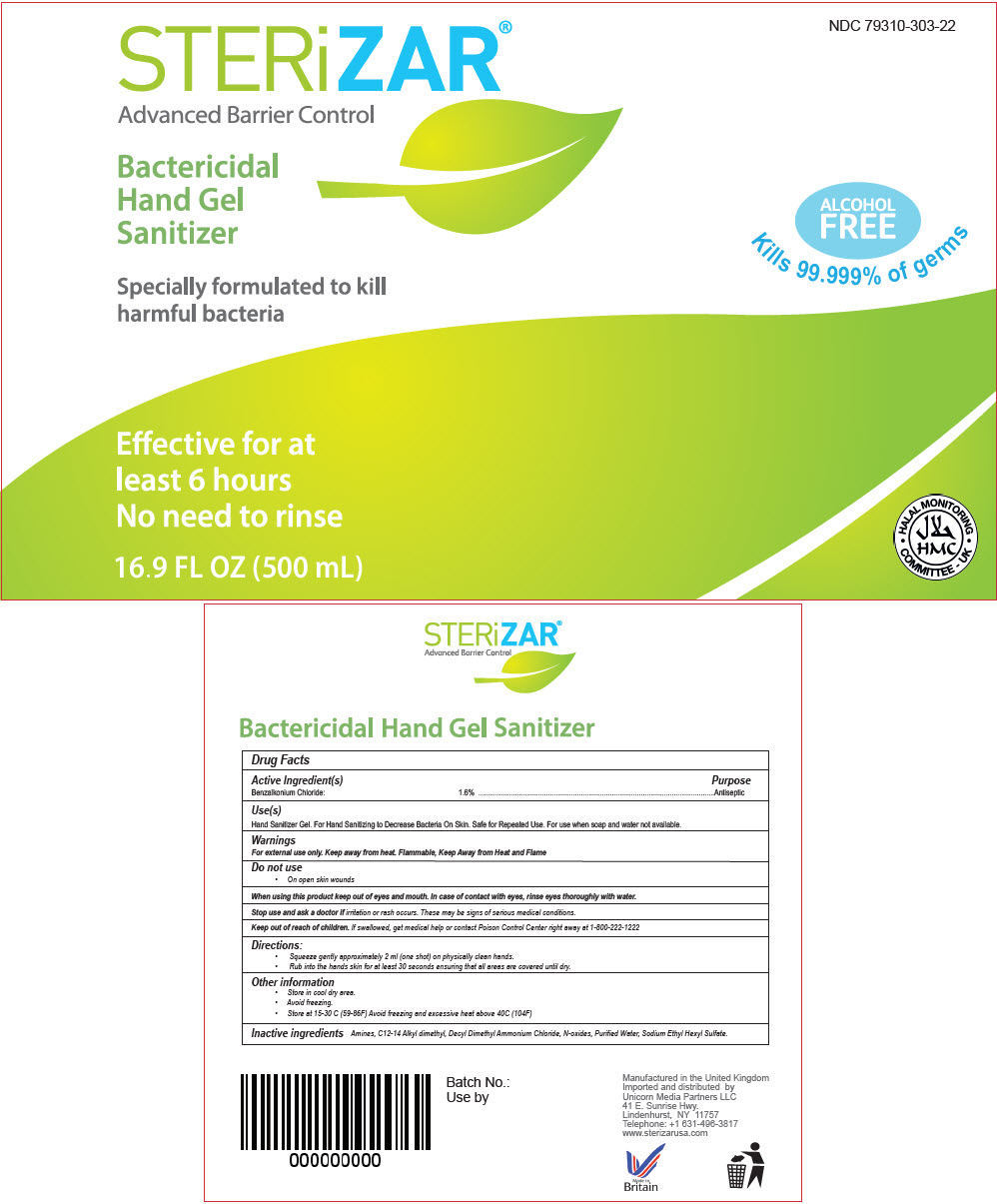 DRUG LABEL: STERiZAR 
NDC: 79310-303 | Form: GEL
Manufacturer: Unicorn Media Partners LLC
Category: otc | Type: HUMAN OTC DRUG LABEL
Date: 20210114

ACTIVE INGREDIENTS: Benzalkonium Chloride 16 mg/1 mL
INACTIVE INGREDIENTS: DIDECYLDIMONIUM CHLORIDE; SODIUM ETHASULFATE; WATER; HYDROXYETHYL CELLULOSE, UNSPECIFIED

STERiZAR®
Advanced Barrier Control

Drug Facts

Active Ingredient(s)

Benzalkonium Chloride: 1.6%

Purpose

Antiseptic

Use(s)

Hand Sanitizer Gel. For Hand Sanitizing to Decrease Bacteria On Skin. Safe for Repeated Use. For use when soap and water not available.

Warnings

For external use only. Keep away from heat. Flammable, Keep Away from Heat and Flame

Do not use

- On open skin wounds

When using this product keep out of eyes and mouth. In case of contact with eyes, rinse eyes thoroughly with water.

Stop use and ask a doctor if irritation or rash occurs. These may be signs of serious medical conditions.

Keep out of reach of children. If swallowed, get medical help or contact Poison Control Center right away at 1-800-222-1222

Directions

- Squeeze gently approximately 2 ml (one shot) on physically clean hands.
- Rub into the hands skin for at least 30 seconds ensuring that all areas are covered until dry.

Other information

- Store in cool dry area.
- Avoid freezing.
- Store at 15-30 C (59-86F) Avoid freezing and excessive heat above 40C (104F)

Inactive ingredients

Amines, C12-14 Alkyl dimethyl, Decyl Dimethyl Ammonium Chloride, N-oxides, Purified Water, Sodium Ethyl Hexyl Sulfate.

Imported and distributed by
Unicorn Media Partners LLC
41 E. Sunrise Hwy.
Lindenhurst, NY 11757

PRINCIPAL DISPLAY PANEL - 500 mL Bottle Label

NDC 79310-303-22

STERiZAR®
Advanced Barrier Control

Bactericidal
Hand Gel
Sanitizer

Specially formulated to kill
harmful bacteria

Effective for at
least 6 hours
No need to rinse

16.9 FL OZ (500 mL)

ALCOHOL
FREE

Kills 99.999% of germs

• HALAL MONITORING •
COMMITTEE - UK